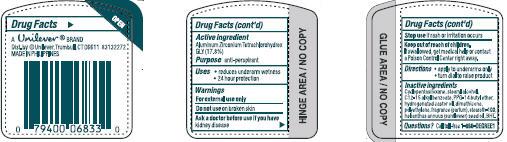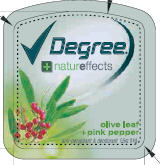 DRUG LABEL: Degree Women
NDC: 64942-1104 | Form: STICK
Manufacturer: Conopco Inc. d/b/a Unilever
Category: otc | Type: HUMAN OTC DRUG LABEL
Date: 20100216

ACTIVE INGREDIENTS: Aluminum Zirconium Tetrachlorohydrex GLY 17.8 g/100 g

Degree Women Nature Effects Honeysuckle and Tea Tree Oil Antiperspirant and Deodorant back and front PACKAGE LABEL.PRINCIPAL DISPLAY PANEL and Drug Facts

Active Ingredient Purpose
Aluminum Zirconium Tetrachlorohydrex GLY (17.8%)............anti-perspirant

Warning
For external use only

Do not use on broken skin

Ask a doctor before use if you have kidney disease

Stop use if rash or irritation occurs.

Keep out of reach of children.

If swallowed, get medical help or contact a Poison Control Center right away

Questions? call 1-866-DEGREE1

Inactive ingredients

Inactive Ingredients Cyclopentasiloxane, Stearyl Alcohol, C12-15 Alkyl Benzoate, PPG-14 Butyl Ether, Hydrogenated Castor Oil, Dimethicone, Polyethylene, Fragrance(Parfum), Steareth-100, Helianthus Annuus (Sunflower) Seed Oil, BHT, Olea Europaea (Olive) Fruit Oil, Schinus Molle Oil [Pink Peppercorn].

PACKAGE LABEL

PDP 0.5 oz. front

PACKAGE LABEL

PDP 0.5 oz back